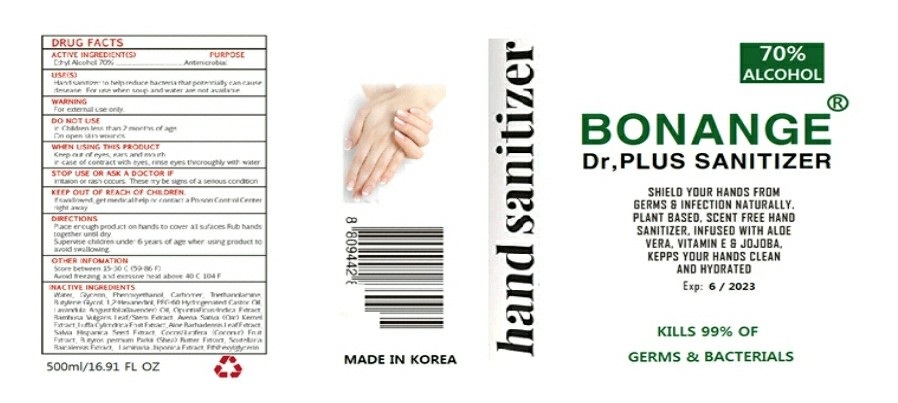 DRUG LABEL: BONANGE Dr,PLUS SANITIZER
NDC: 78761-0002 | Form: GEL
Manufacturer: Bonange Korea Inc
Category: otc | Type: HUMAN OTC DRUG LABEL
Date: 20200605

ACTIVE INGREDIENTS: ALCOHOL 70 mL/100 mL
INACTIVE INGREDIENTS: WATER; TROLAMINE; ALOE VERA LEAF; BUTYLENE GLYCOL; GLYCERIN; PHENOXYETHANOL; CARBOMER 940

Active Ingredient(s)

alcohol

Purpose

Purpose: Antiseptic

Use

 Hand sanitizing to help reduce bacteria on the skin

Warnings

For external use only.
when using this product, avoid contact with the eyes. In case of contact, rinse eyes thoroughly with water.
Stop use and ask a doctor if irritation or redness appears and lasts.

 Keep out of reach of children. If swallowed, get medical help or contact a Poison Control Center immediately.

Directions

• Place enough product on hands to cover all surfaces. Rub hands together until dry.

• Supervise children under 6 years of age when using this product to avoid swallowing.

INACTIVE INGREDIENT

Water

Glycern

Phenoxyethanol

Cabomer

Triethanolamine

Butylene Glycol

1,2-Hexanediol

OpuntiaFicus-Indica Extract

Bambusa Vulgaris Leaf/Stem Extact

AvenaSativa(oat)kemel Ext

Luffa Cylindrica Fruit Ext

Aloe Barbadensis Leaf Ext

Salvia Hispanica Seed Ext

Cocos Nucifera(Coconut)Fruit

ButyrospermumParkil(Shea)Butter Ext

scutellariaBaicalensis Ext

LaminariaJaponica Ext

Ethylhexylglycerin